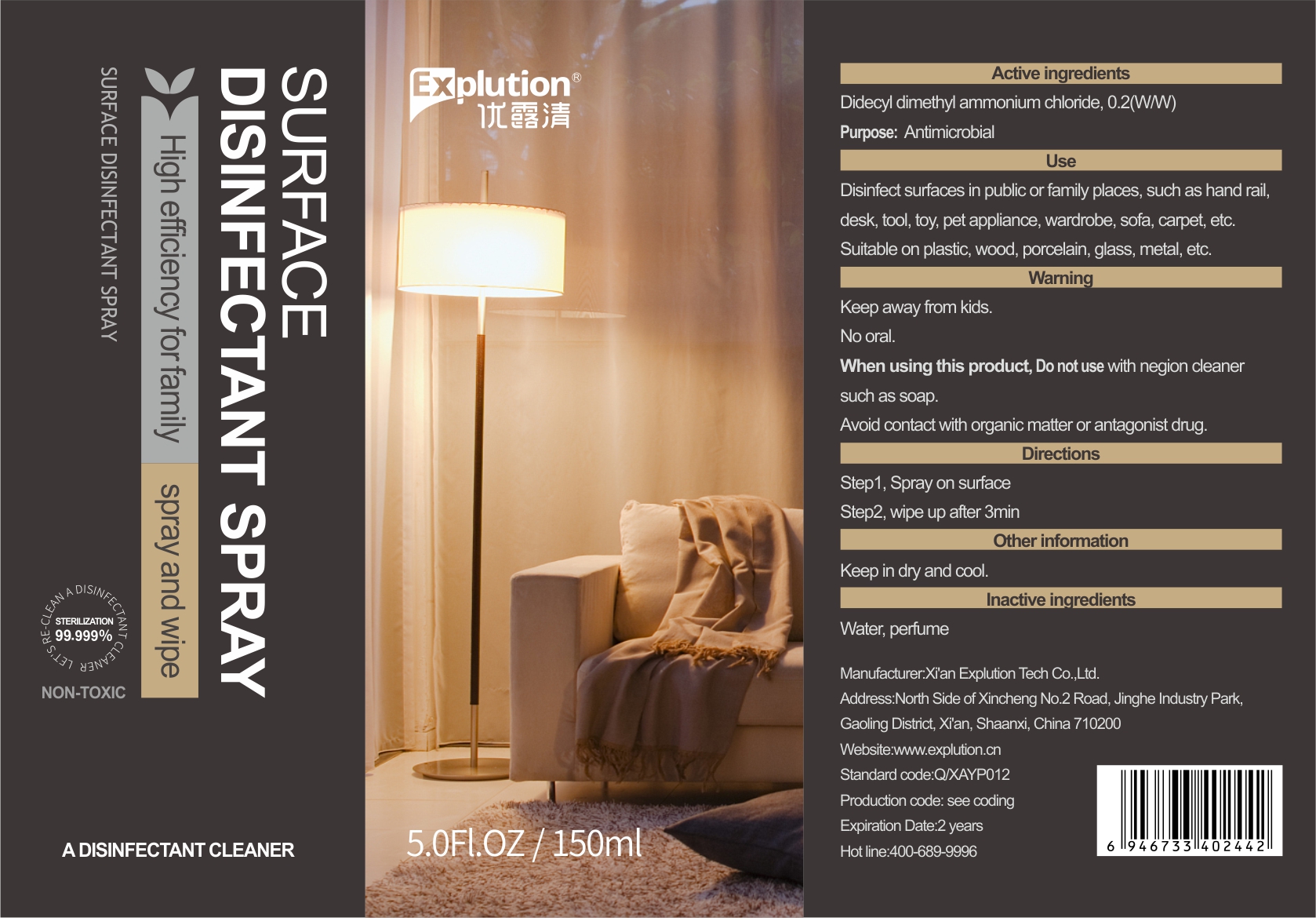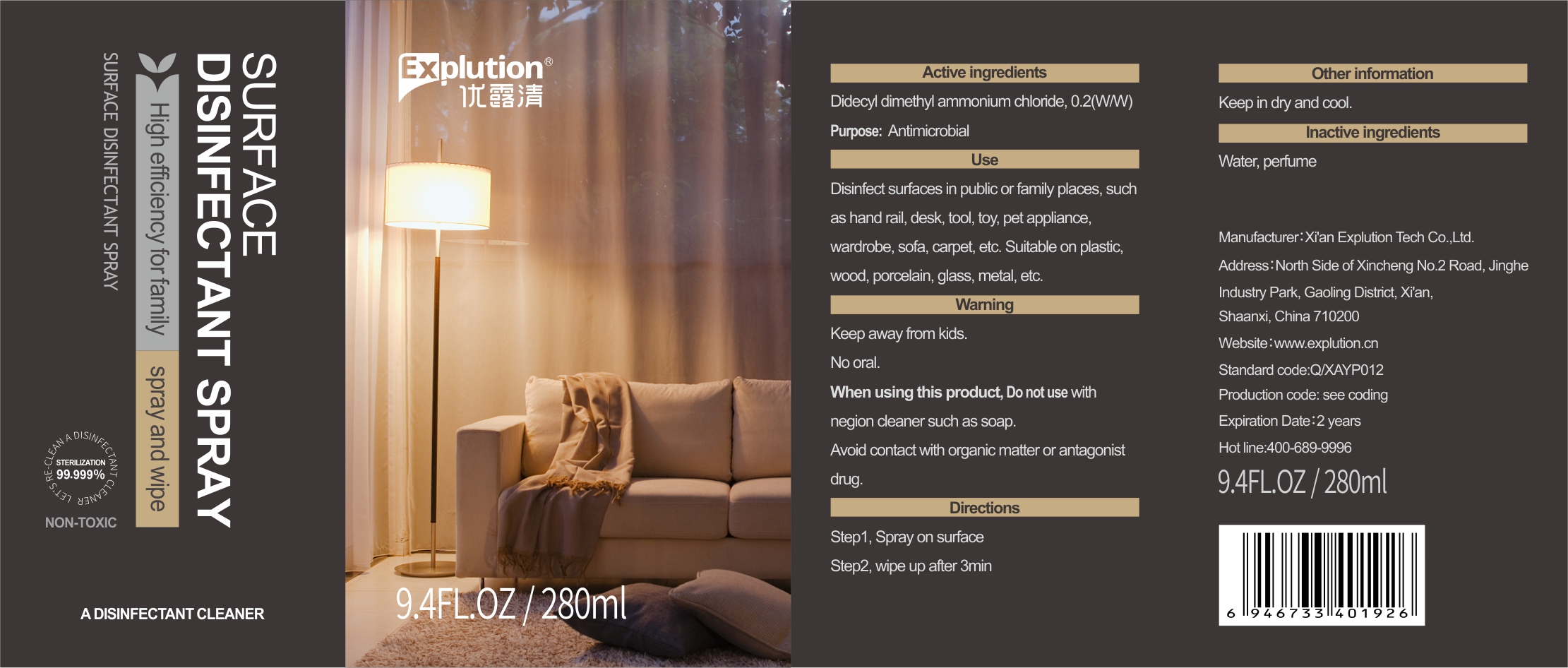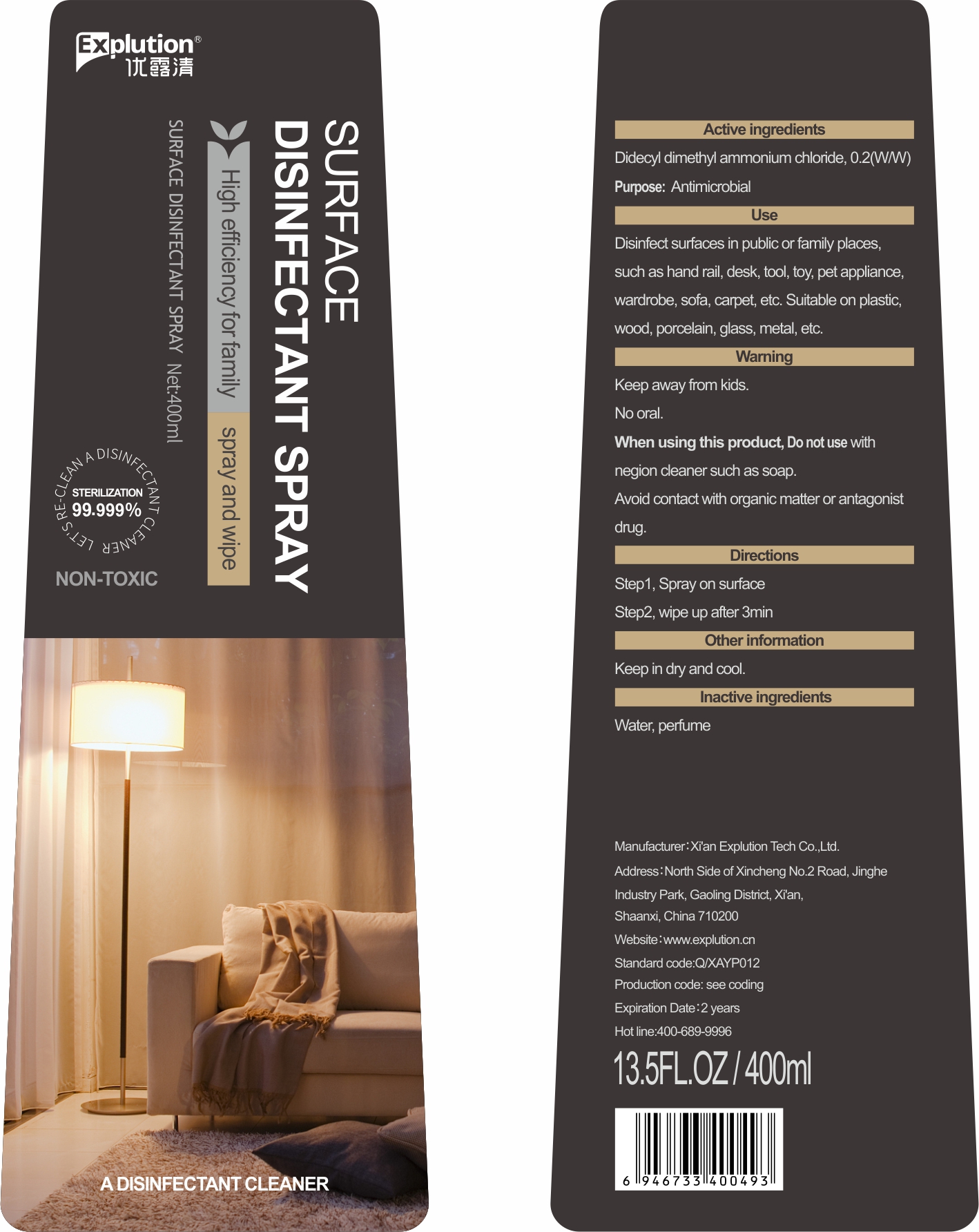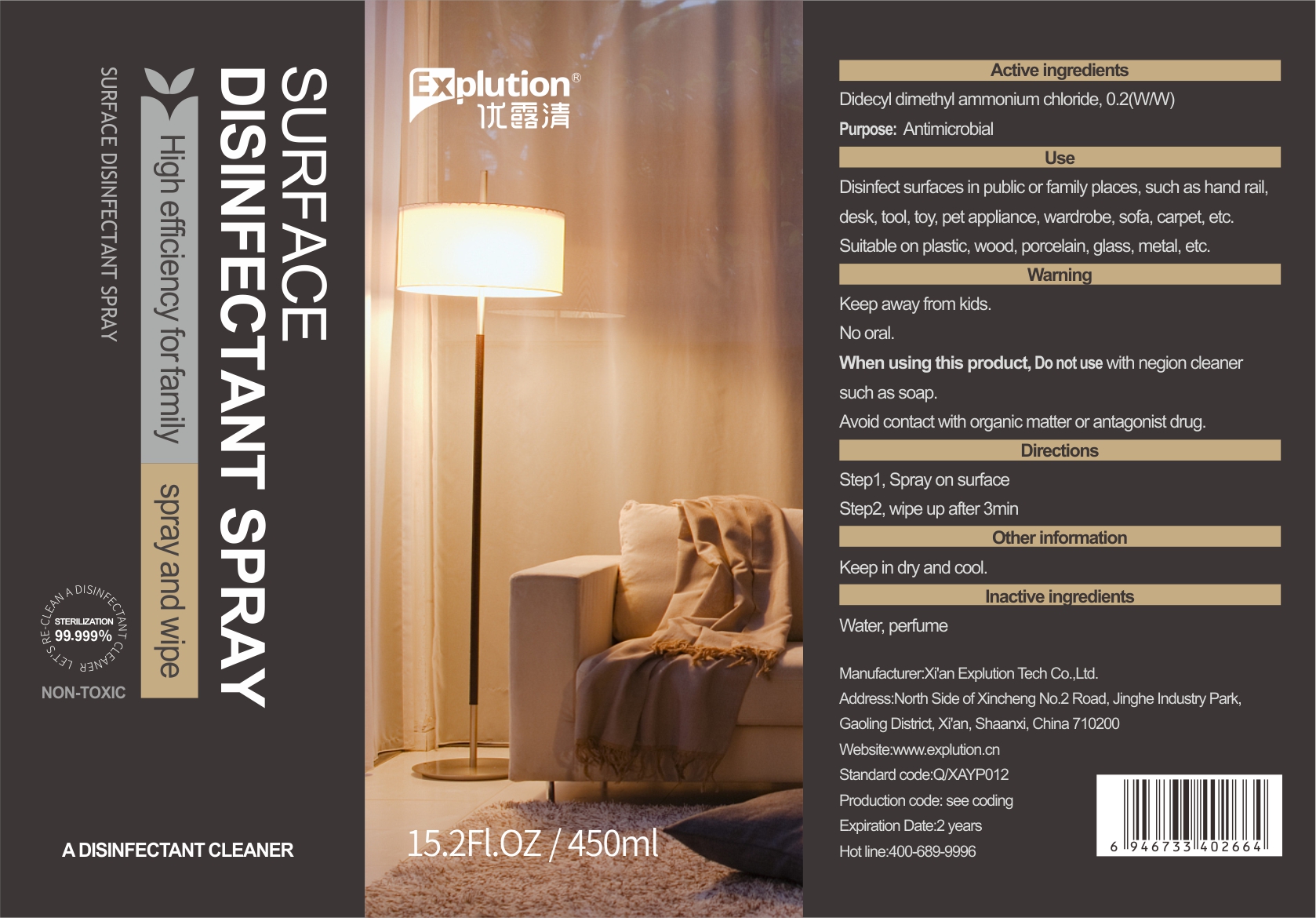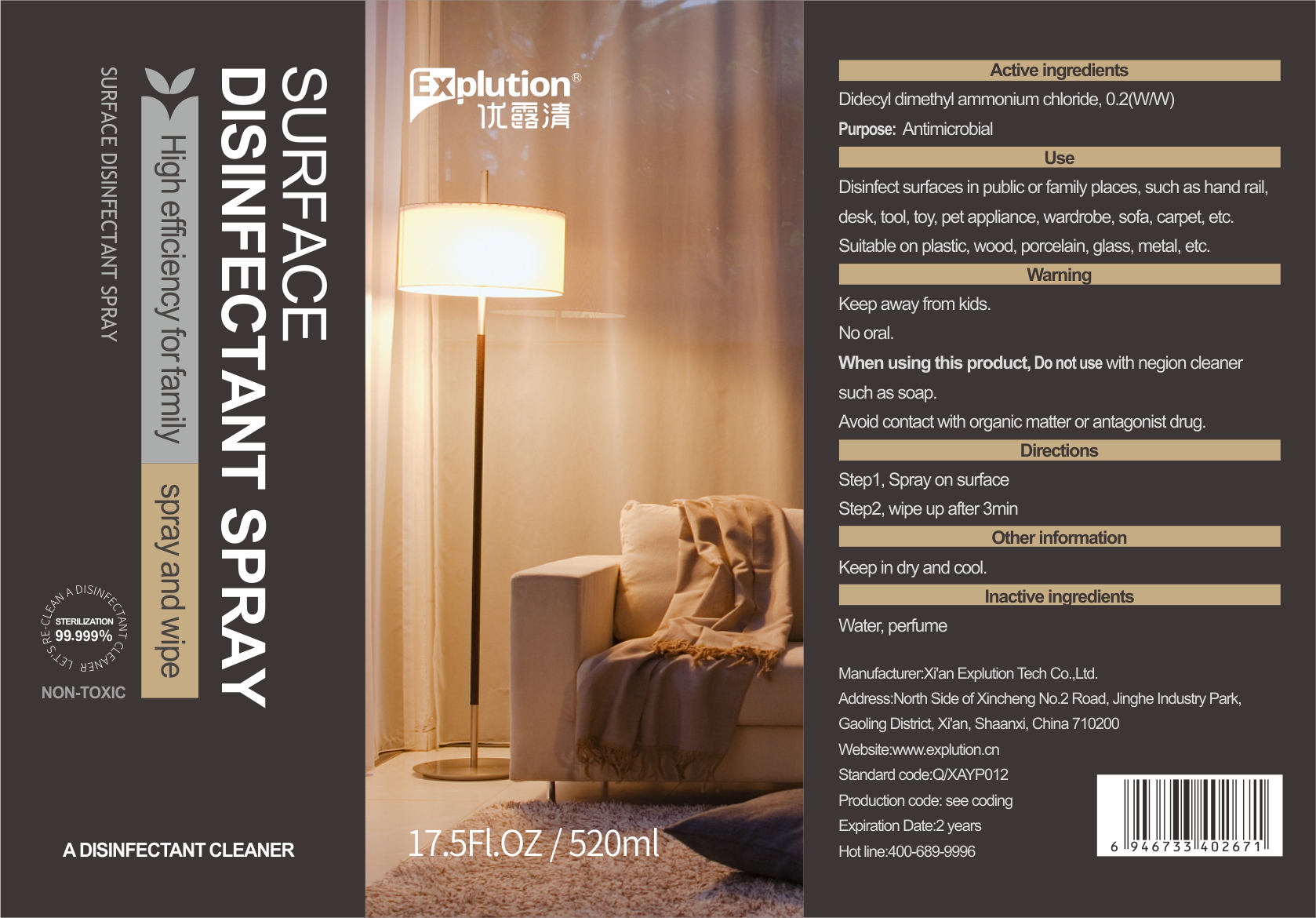 DRUG LABEL: Surface Disinfectant
NDC: 75709-011 | Form: SPRAY
Manufacturer: Xi'an Explution Tech Co.,Ltd.
Category: otc | Type: HUMAN OTC DRUG LABEL
Date: 20200627

ACTIVE INGREDIENTS: DIDECYLDIMONIUM CHLORIDE 0.2 g/100 mL
INACTIVE INGREDIENTS: WATER

Surface Disinfectant Spray

Active ingredients

Didecyl dimethyl ammonium chloride,0.2(WW)

Purpose

Antimicrobial

Use

Disinfect surfaces in public or family places,such as hand rail ,desk,tool, toy, pet appliance,wardrobe, sofa,carpet, etc.Suitable on plastic,wood,porcelain,glass, metal, etc.

Warning

Keep away from kids.No oral.

When using this product

Do not use with negion cleaner such as soap. Avoid contact with organic matter or antagonist drug.

Directions

Step 1, Spray on surface

Step 2, wipe up after 3min

Other information

Keep in dry and cool.

Inactive ingredients

Water,perfume